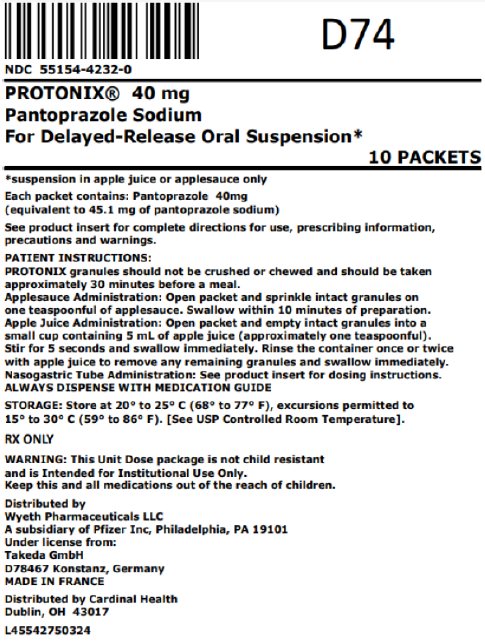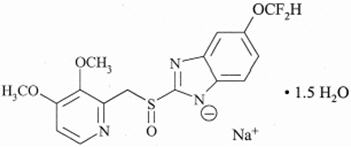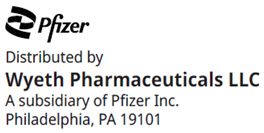 DRUG LABEL: Protonix
NDC: 55154-4232 | Form: GRANULE, DELAYED RELEASE
Manufacturer: Cardinal Health 107, LLC
Category: prescription | Type: HUMAN PRESCRIPTION DRUG LABEL
Date: 20241010

ACTIVE INGREDIENTS: PANTOPRAZOLE SODIUM 40 mg/1 1
INACTIVE INGREDIENTS: CROSPOVIDONE (120 .MU.M); HYPROMELLOSE 2910 (3 MPA.S); HYPROMELLOSE 2910 (5 MPA.S); HYPROMELLOSE 2910 (6 MPA.S); METHACRYLIC ACID AND ETHYL ACRYLATE COPOLYMER; MICROCRYSTALLINE CELLULOSE; POLYSORBATE 80; POVIDONE K25; SODIUM CARBONATE; SODIUM LAURYL SULFATE; TALC; TITANIUM DIOXIDE; TRIETHYL CITRATE; FERRIC OXIDE YELLOW

HIGHLIGHTS OF PRESCRIBING INFORMATION

These highlights do not include all the information needed to use PROTONIX safely and effectively. See full prescribing information for PROTONIX.
PROTONIX (pantoprazole sodium) delayed-release tablets, for oral use
PROTONIX (pantoprazole sodium) for delayed-release oral suspension
Initial U.S. approval: 2000

1 INDICATIONS AND USAGE

PROTONIX is a proton pump inhibitor (PPI) indicated for the following:

- Short-Term Treatment of Erosive Esophagitis Associated with Gastroesophageal Reflux Disease (GERD) (1.1)
- Maintenance of Healing of Erosive Esophagitis (1.2)
- Pathological Hypersecretory Conditions Including Zollinger-Ellison (ZE) Syndrome (1.3)

2 DOSAGE AND ADMINISTRATION

Indication | Dose | Frequency
Short-Term Treatment of Erosive Esophagitis Associated With GERD (2.1)
Adults | 40 mg | Once Daily for up to 8 wks
Children (5 years and older)
≥ 15 kg to < 40 kg | 20 mg | Once Daily for up to 8 wks
≥ 40 kg | 40 mg
Maintenance of Healing of Erosive Esophagitis (2.1)
Adults | 40 mg | Once Daily [Controlled studies did not extend beyond 12 months]
Pathological Hypersecretory Conditions Including Zollinger-Ellison Syndrome (2.1)
Adults | 40 mg | Twice Daily

See full prescribing information for administration instructions

3 DOSAGE FORMS AND STRENGTHS

- Delayed-Release Tablets: 20 mg and 40 mg pantoprazole (3)
- For Delayed-Release Oral Suspension: 40 mg pantoprazole (3)

4 CONTRAINDICATIONS

- Patients with known hypersensitivity to any component of the formulation or to substituted benzimidazoles (4)
- Patients receiving rilpivirine-containing products (4,7)

5 WARNINGS AND PRECAUTIONS

- Gastric Malignancy: In adults, symptomatic response does not preclude presence of gastric malignancy. Consider additional follow-up and diagnostic testing. (5.1)
- Acute Tubulointerstitial Nephritis: Discontinue treatment and evaluate patients. (5.2)
- Clostridium difficile-Associated Diarrhea: PPI therapy may be associated with increased risk of Clostridium difficile-associated diarrhea. (5.3)
- Bone Fracture: Long-term and multiple daily dose PPI therapy may be associated with an increased risk for osteoporosis-related fractures of the hip, wrist or spine. (5.4)
- Severe Cutaneous Adverse Reactions: Discontinue at the first signs or symptoms of severe cutaneous adverse reactions or other signs of hypersensitivity and consider further evaluation. (5.5)
- Cutaneous and Systemic Lupus Erythematosus: Mostly cutaneous; new onset or exacerbation of existing disease; discontinue PROTONIX and refer to specialist for evaluation. (5.6)
- Cyanocobalamin (Vitamin B-12) Deficiency: Daily long-term use (e.g., longer than 3 years) may lead to malabsorption or a deficiency of cyanocobalamin. (5.7)
- Hypomagnesemia and Mineral Metabolism: Reported rarely with prolonged treatment with PPIs. (5.8)
- Fundic Gland Polyps: Risk increases with long-term use, especially beyond one year. Use the shortest duration of therapy. (5.10)

6 ADVERSE REACTIONS

Most common adverse reactions are:

- For adult use (>2%): headache, diarrhea, nausea, abdominal pain, vomiting, flatulence, dizziness, and arthralgia. (6.1)
- For pediatric use (>4%): URI, headache, fever, diarrhea, vomiting, rash, and abdominal pain. (6.1)

To report SUSPECTED ADVERSE REACTIONS, contact Pfizer Inc at 1-800-438-1985 or FDA at 1-800-FDA-1088 or www.fda.gov/medwatch.

7 DRUG INTERACTIONS

See full prescribing information for a list of clinically important drug interactions (7)

8 USE IN SPECIFIC POPULATIONS

Pregnancy: Based on animal data, may cause fetal harm. (8.1)

FULL PRESCRIBING INFORMATION

1 INDICATIONS AND USAGE

PROTONIX For Delayed-Release Oral Suspension and PROTONIX Delayed-Release Tablets are indicated for:

1.1 Short-Term Treatment of Erosive Esophagitis Associated With Gastroesophageal Reflux Disease (GERD)

PROTONIX is indicated in adults and pediatric patients five years of age and older for the short-term treatment (up to 8 weeks) in the healing and symptomatic relief of erosive esophagitis (EE). For those adult patients who have not healed after 8 weeks of treatment, an additional 8-week course of PROTONIX may be considered. Safety of treatment beyond 8 weeks in pediatric patients has not been established.

1.2 Maintenance of Healing of Erosive Esophagitis

PROTONIX is indicated for maintenance of healing of EE and reduction in relapse rates of daytime and nighttime heartburn symptoms in adult patients with GERD. Controlled studies did not extend beyond 12 months.

1.3 Pathological Hypersecretory Conditions Including Zollinger-Ellison Syndrome

PROTONIX is indicated for the long-term treatment of pathological hypersecretory conditions, including Zollinger-Ellison (ZE) Syndrome.

2 DOSAGE AND ADMINISTRATION

2.1 Recommended Dosing Schedule

PROTONIX is supplied as delayed-release granules in packets for preparation of oral suspensions or as delayed-release tablets. The recommended dosages are outlined in Table 1.

Table 1: Recommended Dosing Schedule for PROTONIX
Indication | Dose | Frequency
Short-Term Treatment of Erosive Esophagitis Associated With GERD
Adults | 40 mg | Once daily for up to 8 weeks [For adult patients who have not healed after 8 weeks of treatment, an additional 8-week course of PROTONIX may be considered.]
Children (5 years and older)
≥ 15 kg to < 40 kg | 20 mg | Once daily for up to 8 weeks
≥ 40 kg | 40 mg
Maintenance of Healing of Erosive Esophagitis
Adults | 40 mg | Once daily [Controlled studies did not extend beyond 12 months]
Pathological Hypersecretory Conditions Including Zollinger-Ellison Syndrome
Adults | 40 mg | Twice daily [Dosage regimens should be adjusted to individual patient needs and should continue for as long as clinically indicated. Doses up to 240 mg daily have been administered.]

2.2 Administration Instructions

Directions for method of administration for each dosage form are presented in Table 2.

Table 2: Administration Instructions
Formulation | Route | Instructions [Do not split, chew, or crush PROTONIX Delayed-Release Tablets and PROTONIX For Delayed-Release Oral Suspension.]
Delayed-Release Tablets | Oral | Swallowed whole, with or without food
For Delayed-Release Oral Suspension | Oral | Administered in 1 teaspoonful of applesauce or apple juice approximately 30 minutes prior to a meal
For Delayed-Release Oral Suspension | Nasogastric tube | See instructions below

Take a missed dose as soon as possible. If it is almost time for the next dose, skip the missed dose and take the next dose at the regular scheduled time. Do not take 2 doses at the same time.

PROTONIX Delayed-Release Tablets

Swallow PROTONIX Delayed-Release Tablets whole, with or without food in the stomach. For patients unable to swallow a 40 mg tablet, two 20 mg tablets may be taken. Concomitant administration of antacids does not affect the absorption of PROTONIX Delayed-Release Tablets.

PROTONIX For Delayed-Release Oral Suspension

Administer PROTONIX For Delayed-Release Oral Suspension approximately 30 minutes prior to a meal via oral administration in apple juice or applesauce or nasogastric tube in apple juice only. Because proper pH is necessary for stability, do not administer PROTONIX For Delayed-Release Oral Suspension in liquids other than apple juice, or foods other than applesauce.

Do not divide the 40 mg PROTONIX For Delayed-Release Oral Suspension packet to create a 20 mg dosage for pediatric patients who are unable to take the tablet formulation.

PROTONIX For Delayed-Release Oral Suspension - Oral Administration in Applesauce

- Open packet.
- Sprinkle granules on one teaspoonful of applesauce. DO NOT USE OTHER FOODS OR CRUSH OR CHEW THE GRANULES.
- Take within 10 minutes of preparation.
- Take sips of water to make sure granules are washed down into the stomach. Repeat water sips as necessary.

PROTONIX For Delayed-Release Oral Suspension - Oral Administration in Apple Juice

- Open packet.
- Empty granules into a small cup or teaspoon containing one teaspoon of apple juice.
- Stir for 5 seconds (granules will not dissolve) and swallow immediately.
- To make sure that the entire dose is taken, rinse the container once or twice with apple juice to remove any remaining granules. Swallow immediately.

PROTONIX For Delayed-Release Oral Suspension - Nasogastric (NG) Tube or Gastrostomy Tube Administration

For patients who have a nasogastric tube or gastrostomy tube in place, PROTONIX For Delayed-Release Oral Suspension can be given as follows:

- Remove the plunger from the barrel of a 2 ounce (60 mL) catheter-tip syringe. Discard the plunger.
- Connect the catheter tip of the syringe to a 16 French (or larger) tube.
- Hold the syringe attached to the tubing as high as possible while giving PROTONIX For Delayed-Release Oral Suspension to prevent any bending of the tubing.
- Empty the contents of the packet into the barrel of the syringe.
- Add 10 mL (2 teaspoonfuls) of apple juice and gently tap and/or shake the barrel of the syringe to help rinse the syringe and tube. Repeat at least twice more using the same amount of apple juice (10 mL or 2 teaspoonfuls) each time. No granules should remain in the syringe.

3 DOSAGE FORMS AND STRENGTHS

Delayed-Release Tablets:

- 40 mg pantoprazole, yellow oval biconvex tablets imprinted with PROTONIX (brown ink) on one side
- 20 mg pantoprazole, yellow oval biconvex tablets imprinted with P20 (brown ink) on one side

For Delayed-Release Oral Suspension:

- 40 mg pantoprazole, pale yellowish to dark brownish, enteric-coated granules in a unit dose packet

4 CONTRAINDICATIONS

- PROTONIX is contraindicated in patients with known hypersensitivity to any component of the formulation or any substituted benzimidazole. Hypersensitivity reactions may include anaphylaxis, anaphylactic shock, angioedema, bronchospasm, acute tubulointerstitial nephritis, and urticaria [see Warnings and Precautions (5.2), Adverse Reactions (6)].
- Proton pump inhibitors (PPIs), including PROTONIX, are contraindicated in patients receiving rilpivirine-containing products [see Drug Interactions (7)].

5 WARNINGS AND PRECAUTIONS

5.1 Presence of Gastric Malignancy

In adults, symptomatic response to therapy with PROTONIX does not preclude the presence of gastric malignancy. Consider additional follow-up and diagnostic testing in adult patients who have a suboptimal response or an early symptomatic relapse after completing treatment with a PPI. In older patients, also consider an endoscopy.

5.2 Acute Tubulointerstitial Nephritis

Acute tubulointerstitial nephritis (TIN) has been observed in patients taking PPIs and may occur at any point during PPI therapy. Patients may present with varying signs and symptoms from symptomatic hypersensitivity reactions to non-specific symptoms of decreased renal function (e.g., malaise, nausea, anorexia). In reported case series, some patients were diagnosed on biopsy and in the absence of extra-renal manifestations (e.g., fever, rash or arthralgia). Discontinue PROTONIX and evaluate patients with suspected acute TIN [see Contraindications (4)].

5.3 Clostridium difficile-Associated Diarrhea

Published observational studies suggest that PPI therapy like PROTONIX may be associated with an increased risk of Clostridium difficile associated diarrhea, especially in hospitalized patients. This diagnosis should be considered for diarrhea that does not improve [see Adverse Reactions (6.2)].

Patients should use the lowest dose and shortest duration of PPI therapy appropriate to the condition being treated.

5.4 Bone Fracture

Several published observational studies suggest that PPI therapy may be associated with an increased risk for osteoporosis-related fractures of the hip, wrist, or spine. The risk of fracture was increased in patients who received high-dose, defined as multiple daily doses, and long-term PPI therapy (a year or longer). Patients should use the lowest dose and shortest duration of PPI therapy appropriate to the condition being treated. Patients at risk for osteoporosis-related fractures should be managed according to established treatment guidelines [see Dosage and Administration (2), Adverse Reactions (6.2)].

5.5 Severe Cutaneous Adverse Reactions

Severe cutaneous adverse reactions, including erythema multiforme, Stevens-Johnson syndrome (SJS), toxic epidermal necrolysis (TEN), drug reaction with eosinophilia and systemic symptoms (DRESS), and acute generalized exanthematous pustulosis (AGEP) have been reported in association with the use of PPIs [see Adverse Reactions (6.2)]. Discontinue PROTONIX at the first signs or symptoms of severe cutaneous adverse reactions or other signs of hypersensitivity and consider further evaluation.

5.6 Cutaneous and Systemic Lupus Erythematosus

Cutaneous lupus erythematosus (CLE) and systemic lupus erythematosus (SLE) have been reported in patients taking PPIs, including pantoprazole sodium. These events have occurred as both new onset and an exacerbation of existing autoimmune disease. The majority of PPI-induced lupus erythematous cases were CLE.

The most common form of CLE reported in patients treated with PPIs was subacute CLE (SCLE) and occurred within weeks to years after continuous drug therapy in patients ranging from infants to the elderly. Generally, histological findings were observed without organ involvement.

Systemic lupus erythematosus (SLE) is less commonly reported than CLE in patients receiving PPIs. PPI associated SLE is usually milder than non-drug induced SLE. Onset of SLE typically occurred within days to years after initiating treatment primarily in patients ranging from young adults to the elderly. The majority of patients presented with rash; however, arthralgia and cytopenia were also reported.

Avoid administration of PPIs for longer than medically indicated. If signs or symptoms consistent with CLE or SLE are noted in patients receiving PROTONIX, discontinue the drug and refer the patient to the appropriate specialist for evaluation. Most patients improve with discontinuation of the PPI alone in 4 to 12 weeks. Serological testing (e.g., ANA) may be positive and elevated serological test results may take longer to resolve than clinical manifestations.

5.7 Cyanocobalamin (Vitamin B-12) Deficiency

Generally, daily treatment with any acid-suppressing medications over a long period of time (e.g., longer than 3 years) may lead to malabsorption of cyanocobalamin (Vitamin B-12) caused by hypo- or achlorhydria. Rare reports of cyanocobalamin deficiency occurring with acid-suppressing therapy have been reported in the literature. This diagnosis should be considered if clinical symptoms consistent with cyanocobalamin deficiency are observed.

5.8 Hypomagnesemia and Mineral Metabolism

Hypomagnesemia, symptomatic and asymptomatic, has been reported rarely in patients treated with PPIs for at least three months, and in most cases after a year of therapy. Serious adverse events include tetany, arrhythmias, and seizures. Hypomagnesemia may lead to hypocalcemia and/or hypokalemia and may exacerbate underlying hypocalcemia in at-risk patients. In most patients, treatment of hypomagnesemia required magnesium replacement and discontinuation of the PPI.

For patients expected to be on prolonged treatment or who take PPIs with medications such as digoxin or drugs that may cause hypomagnesemia (e.g., diuretics), health care professionals may consider monitoring magnesium levels prior to initiation of PPI treatment and periodically [see Adverse Reactions (6.2)].

Consider monitoring magnesium and calcium levels prior to initiation of PROTONIX and periodically while on treatment in patients with a preexisting risk of hypocalcemia (e.g., hypoparathyroidism). Supplement with magnesium and/or calcium as necessary. If hypocalcemia is refractory to treatment, consider discontinuing the PPI.

5.9 Tumorigenicity

Due to the chronic nature of GERD, there may be a potential for prolonged administration of PROTONIX. In long-term rodent studies, pantoprazole was carcinogenic and caused rare types of gastrointestinal tumors. The relevance of these findings to tumor development in humans is unknown [see Nonclinical Toxicology (13.1)].

5.10 Fundic Gland Polyps

PPI use is associated with an increased risk of fundic gland polyps that increases with long-term use, especially beyond one year. Most PPI users who developed fundic gland polyps were asymptomatic and fundic gland polyps were identified incidentally on endoscopy. Use the shortest duration of PPI therapy appropriate to the condition being treated.

5.11 Interference with Investigations for Neuroendocrine Tumors

Serum chromogranin A (CgA) levels increase secondary to drug-induced decreases in gastric acidity. The increased CgA level may cause false positive results in diagnostic investigations for neuroendocrine tumors. Healthcare providers should temporarily stop PROTONIX treatment at least 14 days before assessing CgA levels and consider repeating the test if initial CgA levels are high. If serial tests are performed (e.g., for monitoring), the same commercial laboratory should be used for testing, as reference ranges between tests may vary [see Clinical Pharmacology (12.2)].

5.12 Interference with Urine Screen for THC

There have been reports of false-positive urine screening tests for tetrahydrocannabinol (THC) in patients receiving PPIs, including PROTONIX [see Drug Interactions (7)].

5.13 Concomitant Use of PROTONIX with Methotrexate

Literature suggests that concomitant use of PPIs with methotrexate (primarily at high dose; see methotrexate prescribing information) may elevate and prolong serum levels of methotrexate and/or its metabolite, possibly leading to methotrexate toxicities. In high-dose methotrexate administration, a temporary withdrawal of the PPI may be considered in some patients [see Drug Interactions (7)].

6 ADVERSE REACTIONS

The following serious adverse reactions are described below and elsewhere in labeling:

- Acute Tubulointerstitial Nephritis [see Warnings and Precautions (5.2)]
- Clostridium difficile-Associated Diarrhea [see Warnings and Precautions (5.3)]
- Bone Fracture [see Warnings and Precautions (5.4)]
- Severe Cutaneous Adverse Reactions [see Warnings and Precautions (5.5)]
- Cutaneous and Systemic Lupus Erythematosus [see Warnings and Precautions (5.6)]
- Cyanocobalamin (Vitamin B-12) Deficiency [see Warnings and Precautions (5.7)]
- Hypomagnesemia and Mineral Metabolism [see Warnings and Precautions (5.8)]
- Fundic Gland Polyps [see Warnings and Precautions (5.10)]

6.1 Clinical Trials Experience

The adverse reaction profiles for PROTONIX (pantoprazole sodium) For Delayed-Release Oral Suspension and PROTONIX (pantoprazole sodium) Delayed-Release Tablets are similar.

Because clinical trials are conducted under widely varying conditions, adverse reaction rates observed in the clinical trials of a drug cannot be directly compared to rates in the clinical trials of another drug and may not reflect the rates observed in clinical practice.

Adults

Safety in nine randomized comparative US clinical trials in patients with GERD included 1,473 patients on oral PROTONIX (20 mg or 40 mg), 299 patients on an H2-receptor antagonist, 46 patients on another PPI, and 82 patients on placebo. The most frequently occurring adverse reactions are listed in Table 3.

Table 3: Adverse Reactions Reported in Clinical Trials of Adult Patients with GERD at a Frequency of >2%
 | PROTONIX (n=1473) % | Comparators (n=345) % | Placebo (n=82) %
Headache | 12.2 | 12.8 | 8.5
Diarrhea | 8.8 | 9.6 | 4.9
Nausea | 7.0 | 5.2 | 9.8
Abdominal pain | 6.2 | 4.1 | 6.1
Vomiting | 4.3 | 3.5 | 2.4
Flatulence | 3.9 | 2.9 | 3.7
Dizziness | 3.0 | 2.9 | 1.2
Arthralgia | 2.8 | 1.4 | 1.2

Additional adverse reactions that were reported for PROTONIX in clinical trials with a frequency of ≤2% are listed below by body system:

Body as a Whole: allergic reaction, pyrexia, photosensitivity reaction, facial edema

Gastrointestinal: constipation, dry mouth, hepatitis

Hematologic: leukopenia, thrombocytopenia

Metabolic/Nutritional: elevated CK (creatine kinase), generalized edema, elevated triglycerides, liver enzymes elevated

Musculoskeletal: myalgia

Nervous: depression, vertigo

Skin and Appendages: urticaria, rash, pruritus

Special Senses: blurred vision

Pediatric Patients

Safety of PROTONIX in the treatment of EE associated with GERD was evaluated in pediatric patients ages 1 year through 16 years in three clinical trials. Safety trials involved pediatric patients with EE; however, as EE is uncommon in the pediatric population, 249 pediatric patients with endoscopically-proven or symptomatic GERD were also evaluated. All adult adverse reactions to PROTONIX are considered relevant to pediatric patients. In patients ages 1 year through 16 years, the most commonly reported (>4%) adverse reactions include: URI, headache, fever, diarrhea, vomiting, rash, and abdominal pain.

For safety information in patients less than 1 year of age see Use in Specific Populations (8.4).

Additional adverse reactions that were reported for PROTONIX in pediatric patients in clinical trials with a frequency of ≤4% are listed below by body system:

Body as a Whole: allergic reaction, facial edema

Gastrointestinal: constipation, flatulence, nausea

Metabolic/Nutritional: elevated triglycerides, elevated liver enzymes, elevated CK (creatine kinase)

Musculoskeletal: arthralgia, myalgia

Nervous: dizziness, vertigo

Skin and Appendages: urticaria

The following adverse reactions seen in adults in clinical trials were not reported in pediatric patients in clinical trials, but are considered relevant to pediatric patients: photosensitivity reaction, dry mouth, hepatitis, thrombocytopenia, generalized edema, depression, pruritus, leukopenia, and blurred vision.

Zollinger-Ellison (ZE) Syndrome

In clinical studies of ZE Syndrome, adverse reactions reported in 35 patients taking PROTONIX 80 mg/day to 240 mg/day for up to 2 years were similar to those reported in adult patients with GERD.

6.2 Postmarketing Experience

The following adverse reactions have been identified during postapproval use of PROTONIX. Because these reactions are reported voluntarily from a population of uncertain size, it is not always possible to reliably estimate their frequency or establish a causal relationship to drug exposure.

These adverse reactions are listed below by body system:

Gastrointestinal Disorders: fundic gland polyps

General Disorders and Administration Conditions: asthenia, fatigue, malaise

Hematologic: pancytopenia, agranulocytosis

Hepatobiliary Disorders: hepatocellular damage leading to jaundice and hepatic failure

Immune System Disorders: anaphylaxis (including anaphylactic shock), systemic lupus erythematosus

Infections and Infestations: Clostridium difficile associated diarrhea

Investigations: weight changes

Metabolism and Nutritional Disorders: hypomagnesemia, hypocalcemia, hypokalemia, hyponatremia

Musculoskeletal Disorders: rhabdomyolysis, bone fracture

Nervous: ageusia, dysgeusia

Psychiatric Disorders: hallucination, confusion, insomnia, somnolence

Renal and Genitourinary Disorders: acute tubulointerstitial nephritis, erectile dysfunction

Skin and Subcutaneous Tissue Disorders: severe dermatologic reactions (some fatal), including erythema multiforme, SJS/TEN, DRESS, AGEP, angioedema (Quincke's edema) and cutaneous lupus erythematosus

7 DRUG INTERACTIONS

Table 4 includes drugs with clinically important drug interactions and interaction with diagnostics when administered concomitantly with PROTONIX and instructions for preventing or managing them.

Consult the labeling of concomitantly used drugs to obtain further information about interactions with PPIs.

Table 4: Clinically Relevant Interactions Affecting Drugs Co-Administered with PROTONIX and Interactions with Diagnostics
Antiretrovirals
Clinical Impact: | The effect of PPIs on antiretroviral drugs is variable. The clinical importance and the mechanisms behind these interactions are not always known.; - Decreased exposure of some antiretroviral drugs (e.g., rilpivirine atazanavir, and nelfinavir) when used concomitantly with pantoprazole may reduce antiviral effect and promote the development of drug resistance. - Increased exposure of other antiretroviral drugs (e.g., saquinavir) when used concomitantly with pantoprazole may increase toxicity of the antiretroviral drugs. - There are other antiretroviral drugs which do not result in clinically relevant interactions with pantoprazole.
Intervention: | Rilpivirine-containing products: Concomitant use with PROTONIX is contraindicated [see Contraindications (4)]. See prescribing information.; Atazanavir: See prescribing information for atazanavir for dosing information.; Nelfinavir: Avoid concomitant use with PROTONIX. See prescribing information for nelfinavir.; Saquinavir: See the prescribing information for saquinavir and monitor for potential saquinavir toxicities.; Other antiretrovirals: See prescribing information.
Warfarin
Clinical Impact: | Increased INR and prothrombin time in patients receiving PPIs, including pantoprazole, and warfarin concomitantly. Increases in INR and prothrombin time may lead to abnormal bleeding and even death.
Intervention: | Monitor INR and prothrombin time. Dose adjustment of warfarin may be needed to maintain target INR range. See prescribing information for warfarin.
Clopidogrel
Clinical Impact: | Concomitant administration of pantoprazole and clopidogrel in healthy subjects had no clinically important effect on exposure to the active metabolite of clopidogrel or clopidogrel-induced platelet inhibition [see Clinical Pharmacology (12.3)].
Intervention: | No dose adjustment of clopidogrel is necessary when administered with an approved dose of PROTONIX.
Methotrexate
Clinical Impact: | Concomitant use of PPIs with methotrexate (primarily at high dose) may elevate and prolong serum concentrations of methotrexate and/or its metabolite hydroxymethotrexate, possibly leading to methotrexate toxicities. No formal drug interaction studies of high-dose methotrexate with PPIs have been conducted [see Warnings and Precautions (5.13)].
Intervention: | A temporary withdrawal of PROTONIX may be considered in some patients receiving high-dose methotrexate.
Drugs Dependent on Gastric pH for Absorption (e.g., iron salts, erlotinib, dasatinib, nilotinib, mycophenolate mofetil, ketoconazole/itraconazole)
Clinical Impact: | Pantoprazole can reduce the absorption of other drugs due to its effect on reducing intragastric acidity.
Intervention: | Mycophenolate mofetil (MMF): Co-administration of pantoprazole sodium in healthy subjects and in transplant patients receiving MMF has been reported to reduce the exposure to the active metabolite, mycophenolic acid (MPA), possibly due to a decrease in MMF solubility at an increased gastric pH [see Clinical Pharmacology (12.3)]. The clinical relevance of reduced MPA exposure on organ rejection has not been established in transplant patients receiving PROTONIX and MMF. Use PROTONIX with caution in transplant patients receiving MMF. See the prescribing information for other drugs dependent on gastric pH for absorption.
Interactions with Investigations of Neuroendocrine Tumors
Clinical Impact: | CgA levels increase secondary to PPI-induced decreases in gastric acidity. The increased CgA level may cause false positive results in diagnostic investigations for neuroendocrine tumors [see Warnings and Precautions (5.11), Clinical Pharmacology (12.2)].
Intervention: | Temporarily stop PROTONIX treatment at least 14 days before assessing CgA levels and consider repeating the test if initial CgA levels are high. If serial tests are performed (e.g., for monitoring), the same commercial laboratory should be used for testing, as reference ranges between tests may vary.
False Positive Urine Tests for THC
Clinical Impact: | There have been reports of false positive urine screening tests for tetrahydrocannabinol (THC) in patients receiving PPIs [see Warnings and Precautions (5.12)].
Intervention: | An alternative confirmatory method should be considered to verify positive results.

8 USE IN SPECIFIC POPULATIONS

8.1 Pregnancy

Risk Summary

Available data from published observational studies did not demonstrate an association of major malformations or other adverse pregnancy outcomes with pantoprazole.

In animal reproduction studies, no evidence of adverse development outcomes was observed with pantoprazole. Reproduction studies have been performed in rats at oral doses up to 450 mg/kg/day (about 88 times the recommended human dose) and rabbits at oral doses up to 40 mg/kg/day (about 16 times the recommended human dose) with administration of pantoprazole during organogenesis in pregnant animals and have revealed no evidence of harm to the fetus due to pantoprazole in this study (see Data).

A pre-and postnatal development toxicity study in rats with additional endpoints to evaluate the effect on bone development was performed with pantoprazole sodium. Oral pantoprazole doses of 5, 15, and 30 mg/kg/day (approximately 1, 3, and 6 times the human dose of 40 mg/day) were administered to pregnant females from gestation day (GD) 6 through lactation day (LD) 21. Changes in bone morphology were observed in pups exposed to pantoprazole in utero and through milk during the period of lactation as well as by oral dosing from postnatal day (PND) 4 through PND 21 [see Use in Specific Populations (8.4)]. There were no drug-related findings in maternal animals. Advise pregnant women of the potential risk of fetal harm.

The estimated background risk of major birth defects and miscarriage for the indicated population is unknown. All pregnancies have a background risk of birth defect, loss or other adverse outcomes. In the U.S. general population, the estimated background risk of major birth defects and miscarriage in the clinically recognized pregnancies is 2 to 4% and 15 to 20%, respectively.

Data

Human Data

Available data from published observational studies failed to demonstrate an association of adverse pregnancy-related outcomes and pantoprazole use. Methodological limitations of these observational studies cannot definitely establish or exclude any drug-associated risk during pregnancy. In a prospective study by the European Network of Teratology Information Services, outcomes from a group of 53 pregnant women administered median daily doses of 40 mg pantoprazole were compared to a control group of 868 pregnant women who did not take any proton pump inhibitors (PPIs). There was no difference in the rate of major malformations between women exposed to PPIs and the control group, corresponding to a Relative Risk (RR)=0.55, [95% Confidence Interval (CI) 0.08–3.95]. In a population-based retrospective cohort study covering all live births in Denmark from 1996 to 2008, there was no significant increase in major birth defects during analysis of first trimester exposure to pantoprazole in 549 live births. A meta-analysis that compared 1,530 pregnant women exposed to PPIs in at least the first trimester with 133,410 unexposed pregnant women showed no significant increases in risk for congenital malformations or spontaneous abortion with exposure to PPIs (for major malformations OR=1.12 ([95% CI 0.86–1.45] and for spontaneous abortions OR=1.29 [95% CI 0.84–1.97]).

Animal Data

Reproduction studies have been performed in rats at oral pantoprazole doses up to 450 mg/kg/day (about 88 times the recommended human dose based on body surface area) and in rabbits at oral doses up to 40 mg/kg/day (about 16 times the recommended human dose based on body surface area) with administration of pantoprazole sodium during organogenesis in pregnant animals. The studies have revealed no evidence of impaired fertility or harm to the fetus due to pantoprazole.

A pre- and postnatal development toxicity study in rats with additional endpoints to evaluate the effect on bone development was performed with pantoprazole sodium. Oral pantoprazole doses of 5, 15, and 30 mg/kg/day (approximately 1, 3, and 6 times the human dose of 40 mg/day on a body surface area basis) were administered to pregnant females from gestation day (GD) 6 through lactation day (LD) 21. On postnatal day (PND 4) through PND 21, the pups were administered oral doses at 5, 15, and 30 mg/kg/day (approximately 1, 2.3, and 3.2 times the exposure (AUC) in humans at a dose of 40 mg). There were no drug-related findings in maternal animals. During the preweaning dosing phase (PND 4 to 21) of the pups, there were increased mortality and/or moribundity and decreased body weight and body weight gain at 5 mg/kg/day (approximately equal exposures (AUC) in humans receiving the 40 mg dose) and higher doses. On PND 21, decreased mean femur length and weight and changes in femur bone mass and geometry were observed in the offspring at 5 mg/kg/day (approximately equal exposures (AUC) in humans at the 40 mg dose) and higher doses. The femur findings included lower total area, bone mineral content and density, periosteal and endosteal circumference, and cross-sectional moment of inertia. There were no microscopic changes in the distal femur, proximal tibia, or stifle joints. Changes in bone parameters were partially reversible following a recovery period, with findings on PND 70 limited to lower femur metaphysis cortical/subcortical bone mineral density in female pups at 5 mg/kg/day (approximately equal exposures (AUC) in humans at the 40 mg dose) and higher doses.

8.2 Lactation

Risk Summary

Pantoprazole has been detected in breast milk of a nursing mother after a single 40 mg oral dose of pantoprazole. There were no effects on the breastfed infant (see Data). There are no data on pantoprazole effects on milk production.

The developmental and health benefits of breastfeeding should be considered along with the mother's clinical need for PROTONIX and any potential adverse effects on the breastfed child from pantoprazole or from the underlying maternal condition.

Data

The breast milk of a 42-year-old woman receiving 40 mg of oral pantoprazole, at 10 months postpartum, was studied for 24 hours, to demonstrate low levels of pantoprazole present in the breast milk. Pantoprazole was detectable in milk only 2 and 4 hours after the dose with milk levels of approximately 36 mcg/L and 24 mcg/L, respectively. A milk-to-plasma ratio of 0.022 was observed at 2 hours after drug administration. Pantoprazole was not detectable (<10 mcg/L) in milk at 6, 8 and 24 hours after the dose. The relative dose to the infant was estimated to be 7.3 mcg of pantoprazole, which is equivalent to 0.14% of the weight-adjusted maternal dose. No adverse events in the infant were reported by the mother.

8.4 Pediatric Use

The safety and effectiveness of PROTONIX for short-term treatment (up to eight weeks) of EE associated with GERD have been established in pediatric patients 1 year through 16 years of age. Effectiveness for EE has not been demonstrated in patients less than 1 year of age. In addition, for patients less than 5 years of age, there is no appropriate dosage strength in an age-appropriate formulation available. Therefore, PROTONIX is indicated for the short-term treatment of EE associated with GERD for patients 5 years and older. The safety and effectiveness of PROTONIX for pediatric uses other than EE have not been established.

1 year through 16 years of age

Use of PROTONIX in pediatric patients 1 year through 16 years of age for short-term treatment (up to eight weeks) of EE associated with GERD is supported by: a) extrapolation of results from adequate and well-controlled studies that supported the approval of PROTONIX for treatment of EE associated with GERD in adults, and b) safety, effectiveness, and pharmacokinetic studies performed in pediatric patients [see Clinical Studies (14.1), Clinical Pharmacology (12.3)].

Safety of PROTONIX in the treatment of EE associated with GERD in pediatric patients 1 through 16 years of age was evaluated in three multicenter, randomized, double-blind, parallel-treatment studies, involving 249 pediatric patients, including 8 with EE (4 patients ages 1 year to 5 years and 4 patients 5 years to 11 years). The children ages 1 year to 5 years with endoscopically diagnosed EE (defined as an endoscopic Hetzel-Dent score ≥2) were treated once daily for 8 weeks with one of two dose levels of PROTONIX (approximating 0.6 mg/kg or 1.2 mg/kg). All 4 of these patients with EE were healed (Hetzel-Dent score of 0 or 1) at 8 weeks. Because EE is uncommon in the pediatric population, predominantly pediatric patients with endoscopically-proven or symptomatic GERD were also included in these studies. Patients were treated with a range of doses of PROTONIX once daily for 8 weeks. For safety findings see Adverse Reactions (6.1). Because these pediatric trials had no placebo, active comparator, or evidence of a dose response, the trials were inconclusive regarding the clinical benefit of PROTONIX for symptomatic GERD in the pediatric population. The effectiveness of PROTONIX for treating symptomatic GERD in pediatric patients has not been established.

Although the data from the clinical trials support use of PROTONIX for the short-term treatment of EE associated with GERD in pediatric patients 1 year through 5 years, there is no commercially available dosage formulation appropriate for patients less than 5 years of age [see Dosage and Administration (2)].

In a population pharmacokinetic analysis, clearance values in the children 1 to 5 years old with endoscopically proven GERD had a median value of 2.4 L/h. Following a 1.2 mg/kg equivalent dose (15 mg for ≤12.5 kg and 20 mg for >12.5 to <25 kg), the plasma concentrations of pantoprazole were highly variable and the median time to peak plasma concentration was 3 to 6 hours. The estimated AUC for patients 1 to 5 years old was 37% higher than for adults receiving a single 40 mg tablet, with a geometric mean AUC value of 6.8 µg∙hr/mL.

Neonates to less than one year of age

PROTONIX was not found to be effective in a multicenter, randomized, double-blind, placebo-controlled, treatment-withdrawal study of 129 pediatric patients 1 through 11 months of age. Patients were enrolled if they had symptomatic GERD based on medical history and had not responded to non-pharmacologic interventions for GERD for two weeks. Patients received PROTONIX daily for four weeks in an open-label phase, then patients were randomized in equal proportion to receive PROTONIX treatment or placebo for the subsequent four weeks in a double-blind manner. Efficacy was assessed by observing the time from randomization to study discontinuation due to symptom worsening during the four-week treatment-withdrawal phase. There was no statistically significant difference between PROTONIX and placebo in the rate of discontinuation.

In this trial, the adverse reactions that were reported more commonly (difference of ≥4%) in the treated population compared to the placebo population were elevated CK, otitis media, rhinitis, and laryngitis.

In a population pharmacokinetic analysis, the systemic exposure was higher in patients less than 1 year of age with GERD compared to adults who received a single 40 mg dose (geometric mean AUC was 103% higher in preterm infants and neonates receiving single dose of 2.5 mg of PROTONIX, and 23% higher in infants 1 through 11 months of age receiving a single dose of approximately 1.2 mg/kg). In these patients, the apparent clearance (CL/F) increased with age (median clearance: 0.6 L/hr, range: 0.03 to 3.2 L/hr).

These doses resulted in pharmacodynamic effects on gastric but not esophageal pH. Following once daily dosing of 2.5 mg of PROTONIX in preterm infants and neonates, there was an increase in the mean gastric pH (from 4.3 at baseline to 5.2 at steady-state) and in the mean % time that gastric pH was > 4 (from 60% at baseline to 80% at steady-state). Following once daily dosing of approximately 1.2 mg/kg of PROTONIX in infants 1 through 11 months of age, there was an increase in the mean gastric pH (from 3.1 at baseline to 4.2 at steady-state) and in the mean % time that gastric pH was > 4 (from 32% at baseline to 60% at steady-state). However, no significant changes were observed in mean intraesophageal pH or % time that esophageal pH was <4 in either age group.

Because PROTONIX was not shown to be effective in the randomized, placebo-controlled study in this age group, the use of PROTONIX for treatment of symptomatic GERD in infants less than 1 year of age is not indicated.

Animal Toxicity Data

In a pre- and post-natal development study in rats, the pups were administered oral doses of pantoprazole at 5, 15, and 30 mg/kg/day (approximately 1, 2.3, and 3.2 times the exposure (AUC) in children aged 6 to 11 years at a dose of 40 mg) on postnatal day (PND 4) through PND 21, in addition to lactational exposure through milk. On PND 21, decreased mean femur length and weight and changes in femur bone mass and geometry were observed in the offspring at 5 mg/kg/day (approximately equal exposures (AUC) in children aged 6 to 11 years at the 40 mg dose) and higher doses. Changes in bone parameters were partially reversible following a recovery period.

In neonatal/juvenile animals (rats and dogs) toxicities were similar to those observed in adult animals, including gastric alterations, decreases in red cell mass, increases in lipids, enzyme induction and hepatocellular hypertrophy. An increased incidence of eosinophilic chief cells in adult and neonatal/juvenile rats, and atrophy of chief cells in adult rats and in neonatal/juvenile dogs, was observed in the fundic mucosa of stomachs in repeated-dose studies. Full to partial recovery of these effects were noted in animals of both age groups following a recovery period.

8.5 Geriatric Use

In short-term US clinical trials, EE healing rates in the 107 elderly patients (≥65 years old) treated with PROTONIX were similar to those found in patients under the age of 65. The incidence rates of adverse reactions and laboratory abnormalities in patients aged 65 years and older were similar to those associated with patients younger than 65 years of age.

10 OVERDOSAGE

Experience in patients taking very high doses of PROTONIX (greater than 240 mg) is limited. Spontaneous post-marketing reports of overdose are generally within the known safety profile of PROTONIX.

Pantoprazole is not removed by hemodialysis. In case of overdosage, treatment should be symptomatic and supportive.

Single oral doses of pantoprazole at 709 mg/kg, 798 mg/kg, and 887 mg/kg were lethal to mice, rats, and dogs, respectively. The symptoms of acute toxicity were hypoactivity, ataxia, hunched sitting, limb-splay, lateral position, segregation, absence of ear reflex, and tremor.

If overexposure to PROTONIX occurs, call your Poison Control Center at 1-800-222-1222 for current information on the management of poisoning or overdosage.

11 DESCRIPTION

The active ingredient in PROTONIX (pantoprazole sodium) For Delayed-Release Oral Suspension and PROTONIX (pantoprazole sodium) Delayed-Release Tablets, a PPI, is a substituted benzimidazole, sodium 5-(difluoromethoxy)-2-[[(3,4-dimethoxy-2-pyridinyl)methyl] sulfinyl]-1H-benzimidazole sesquihydrate, a compound that inhibits gastric acid secretion. Its empirical formula is C16H14F2N3NaO4S × 1.5 H2O, with a molecular weight of 432.4. The structural formula is:

Pantoprazole sodium sesquihydrate is a white to off-white crystalline powder and is racemic. Pantoprazole has weakly basic and acidic properties. Pantoprazole sodium sesquihydrate is freely soluble in water, very slightly soluble in phosphate buffer at pH 7.4, and practically insoluble in n-hexane.

The stability of the compound in aqueous solution is pH-dependent. The rate of degradation increases with decreasing pH. At ambient temperature, the degradation half-life is approximately 2.8 hours at pH 5 and approximately 220 hours at pH 7.8.

PROTONIX is supplied as a for delayed-release oral suspension in unit dose packets, available in one strength 40 mg pantoprazole, (equivalent to 45.1 mg of pantoprazole sodium), and as a delayed-release tablet, available in two strengths 20 mg pantoprazole (equivalent to 22.56 mg of pantoprazole sodium) and 40 mg pantoprazole (equivalent to 45.1 mg of pantoprazole sodium).

PROTONIX Delayed-Release Tablets contains the following inactive ingredients: calcium stearate, crospovidone, hypromellose, iron oxide, mannitol, methacrylic acid copolymer, polysorbate 80, povidone, propylene glycol, sodium carbonate, sodium lauryl sulfate, titanium dioxide, and triethyl citrate. PROTONIX Delayed-Release Tablets (40 mg and 20 mg) complies with USP dissolution test 2.

PROTONIX For Delayed-Release Oral Suspension contains the following inactive ingredients: crospovidone, hypromellose, methacrylic acid copolymer, microcrystalline cellulose, polysorbate 80, povidone, sodium carbonate, sodium lauryl sulfate, talc, titanium dioxide, triethyl citrate, and yellow ferric oxide.

12 CLINICAL PHARMACOLOGY

12.1 Mechanism of Action

Pantoprazole is a PPI that suppresses the final step in gastric acid production by covalently binding to the (H^+, K^+)-ATPase enzyme system at the secretory surface of the gastric parietal cell. This effect leads to inhibition of both basal and stimulated gastric acid secretion, irrespective of the stimulus. The binding to the (H^+, K^+)-ATPase results in a duration of antisecretory effect that persists longer than 24 hours for all doses tested (20 mg to 120 mg).

12.2 Pharmacodynamics

PROTONIX For Delayed-Release Oral Suspension, 40 mg has been shown to be comparable to PROTONIX Delayed-Release Tablets in suppressing pentagastrin-stimulated MAO in patients (n = 49) with GERD and a history of EE. In this multicenter, pharmacodynamic crossover study, a 40 mg oral dose of PROTONIX For Delayed-Release Oral Suspension administered in a teaspoonful of applesauce was compared with a 40 mg oral dose of PROTONIX Delayed-Release Tablets after administration of each formulation once daily for 7 days. Both medications were administered thirty minutes before breakfast. Pentagastrin-stimulated (MAO) was assessed from hour 23 to 24 at steady state.

Antisecretory Activity

Under maximal acid stimulatory conditions using pentagastrin, a dose-dependent decrease in gastric acid output occurs after a single dose of oral (20–80 mg) or a single dose of intravenous (20–120 mg) pantoprazole in healthy subjects. Pantoprazole given once daily results in increasing inhibition of gastric acid secretion. Following the initial oral dose of 40 mg pantoprazole, a 51% mean inhibition was achieved by 2.5 hours. With once-a-day dosing for 7 days, the mean inhibition was increased to 85%. Pantoprazole suppressed acid secretion in excess of 95% in half of the subjects. Acid secretion had returned to normal within a week after the last dose of pantoprazole; there was no evidence of rebound hypersecretion.

In a series of dose-response studies, pantoprazole, at oral doses ranging from 20 to 120 mg, caused dose-related increases in median basal gastric pH and in the percent of time gastric pH was >3 and >4. Treatment with 40 mg of pantoprazole produced significantly greater increases in gastric pH than the 20 mg dose. Doses higher than 40 mg (60, 80, 120 mg) did not result in further significant increases in median gastric pH. The effects of pantoprazole on median pH from one double-blind crossover study are shown in Table 5.

Table 5: Effect of Single Daily Doses of Oral Pantoprazole on Intragastric pH
 | Median pH on day 7
Time | Placebo | 20 mg | 40 mg | 80 mg
8 a.m. – 8 a.m. (24 hours) | 1.3 | 2.9 [Significantly different from placebo] | 3.8 [Significantly different from 20 mg] | 3.9
8 a.m. – 10 p.m. (Daytime) | 1.6 | 3.2 | 4.4 | 4.8
10 p.m. – 8 a.m. (Nighttime) | 1.2 | 2.1 | 3.0 | 2.6

Serum Gastrin Effects

Fasting serum gastrin levels were assessed in two double-blind studies of the acute healing of EE in which 682 patients with gastroesophageal reflux disease (GERD) received 10, 20, or 40 mg of PROTONIX for up to 8 weeks. At 4 weeks of treatment there was an increase in mean gastrin levels of 7%, 35%, and 72% over pretreatment values in the 10, 20, and 40 mg treatment groups, respectively. A similar increase in serum gastrin levels was noted at the 8-week visit with mean increases of 3%, 26%, and 84% for the three pantoprazole dose groups. Median serum gastrin levels remained within normal limits during maintenance therapy with PROTONIX Delayed-Release Tablets.

In long-term international studies involving over 800 patients, a 2- to 3-fold mean increase from the pretreatment fasting serum gastrin level was observed in the initial months of treatment with pantoprazole at doses of 40 mg per day during GERD maintenance studies and 40 mg or higher per day in patients with refractory GERD. Fasting serum gastrin levels generally remained at approximately 2 to 3 times baseline for up to 4 years of periodic follow-up in clinical trials.

Following short-term treatment with PROTONIX, elevated gastrin levels return to normal by at least 3 months.

Enterochromaffin-Like (ECL) Cell Effects

In 39 patients treated with oral pantoprazole 40 mg to 240 mg daily (majority receiving 40 mg to 80 mg) for up to 5 years, there was a moderate increase in ECL-cell density, starting after the first year of use, which appeared to plateau after 4 years.

In a nonclinical study in Sprague-Dawley rats, lifetime exposure (24 months) to pantoprazole at doses of 0.5 to 200 mg/kg/day resulted in dose-related increases in gastric ECL-cell proliferation and gastric neuroendocrine (NE)-cell tumors. Gastric NE-cell tumors in rats may result from chronic elevation of serum gastrin concentrations. The high density of ECL cells in the rat stomach makes this species highly susceptible to the proliferative effects of elevated gastrin concentrations produced by PPIs. However, there were no observed elevations in serum gastrin following the administration of pantoprazole at a dose of 0.5 mg/kg/day. In a separate study, a gastric NE-cell tumor without concomitant ECL-cell proliferative changes was observed in 1 female rat following 12 months of dosing with pantoprazole at 5 mg/kg/day and a 9 month off-dose recovery [see Nonclinical Toxicology (13.1)].

Endocrine Effects

In a clinical pharmacology study, PROTONIX 40 mg given once daily for 2 weeks had no effect on the levels of the following hormones: cortisol, testosterone, triiodothyronine (T3), thyroxine (T4), thyroid-stimulating hormone (TSH), thyronine-binding protein, parathyroid hormone, insulin, glucagon, renin, aldosterone, follicle-stimulating hormone, luteinizing hormone, prolactin, and growth hormone.

In a 1-year study of GERD patients treated with PROTONIX 40 mg or 20 mg, there were no changes from baseline in overall levels of T3, T4, and TSH.

12.3 Pharmacokinetics

PROTONIX Delayed-Release Tablets are prepared as enteric-coated tablets so that absorption of pantoprazole begins only after the tablet leaves the stomach. Peak serum concentration (Cmax) and area under the serum concentration time curve (AUC) increase in a manner proportional to oral and intravenous doses from 10 mg to 80 mg. Pantoprazole does not accumulate, and its pharmacokinetics are unaltered with multiple daily dosing. Following oral or intravenous administration, the serum concentration of pantoprazole declines biexponentially, with a terminal elimination half-life of approximately one hour.

In extensive metabolizers with normal liver function receiving an oral dose of the enteric-coated 40 mg pantoprazole tablet, the peak concentration (Cmax) is 2.5 μg/mL; the time to reach the peak concentration (tmax) is 2.5 h, and the mean total area under the plasma concentration versus time curve (AUC) is 4.8 μg∙h/mL (range 1.4 to 13.3 μg∙h/mL). Following intravenous administration of pantoprazole to extensive metabolizers, its total clearance is 7.6–14.0 L/h, and its apparent volume of distribution is 11.0–23.6 L.

A single oral dose of PROTONIX For Delayed-Release Oral Suspension, 40 mg, was shown to be bioequivalent when administered to healthy subjects (N = 22) as granules sprinkled over a teaspoonful of applesauce, as granules mixed with apple juice, or mixed with apple juice followed by administration through a nasogastric tube. The plasma pharmacokinetic parameters from a crossover study in healthy subjects are summarized in Table 6.

Table 6: Pharmacokinetics Parameters (mean ± SD) of PROTONIX For Delayed-Release Oral Suspension at 40 mg
Pharmacokinetic Parameters | Granules in Applesauce | Granules in Apple Juice | Granules in Nasogastric Tube
AUC (µg∙hr/mL) | 4.0 ± 1.5 | 4.0 ± 1.5 | 4.1 ± 1.7
Cmax (µg/mL) | 2.0 ± 0.7 | 1.9 ± 0.5 | 2.2 ± 0.7
Tmax (hr) [Median values are reported for Tmax.] | 2.0 | 2.5 | 2.0

Absorption

After administration of a single or multiple oral 40 mg doses of PROTONIX Delayed-Release Tablets, the peak plasma concentration of pantoprazole was achieved in approximately 2.5 hours, and Cmax was 2.5 μg/mL. Pantoprazole undergoes little first-pass metabolism, resulting in an absolute bioavailability of approximately 77%. Pantoprazole absorption is not affected by concomitant administration of antacids.

Administration of PROTONIX Delayed-Release Tablets with food may delay its absorption up to 2 hours or longer; however, the Cmax and the extent of pantoprazole absorption (AUC) are not altered. Thus, PROTONIX Delayed-Release Tablets may be taken without regard to timing of meals.

Administration of pantoprazole granules, 40 mg, with a high-fat meal delayed median time to peak plasma concentration by 2 hours. With a concomitant high-fat meal, the Cmax and AUC of pantoprazole granules, 40 mg, sprinkled on applesauce decreased by 51% and 29%, respectively. Thus, PROTONIX For Delayed-Release Oral Suspension should be taken approximately 30 minutes before a meal.

Distribution

The apparent volume of distribution of pantoprazole is approximately 11 to 23.6 L, distributing mainly in extracellular fluid. The serum protein binding of pantoprazole is about 98%, primarily to albumin.

Elimination

Metabolism

Pantoprazole is extensively metabolized in the liver through the cytochrome P450 (CYP) system. Pantoprazole metabolism is independent of the route of administration (intravenous or oral). The main metabolic pathway is demethylation, by CYP2C19, with subsequent sulfation; other metabolic pathways include oxidation by CYP3A4. There is no evidence that any of the pantoprazole metabolites have significant pharmacologic activity.

Excretion

After a single oral or intravenous dose of ^14C-labeled pantoprazole to healthy, normal metabolizer subjects, approximately 71% of the dose was excreted in the urine, with 18% excreted in the feces through biliary excretion. There was no renal excretion of unchanged pantoprazole.

Specific Populations

Geriatric Patients

Only slight to moderate increases in the AUC (43%) and Cmax (26%) of pantoprazole were found in elderly subjects (64 to 76 years of age) after repeated oral administration, compared with younger subjects [see Use in Specific Populations (8.5)].

Pediatric Patients

The pharmacokinetics of pantoprazole were studied in children less than 16 years of age in four randomized, open-label clinical trials in pediatric patients with presumed/proven GERD. A pediatric granule formulation was studied in children through 5 years of age, and PROTONIX Delayed-Release Tablets were studied in children older than 5 years.

In a population PK analysis, total clearance increased with increasing bodyweight in a non-linear fashion. The total clearance also increased with increasing age only in children under 3 years of age.

Neonate through 5 Years of Age

[see Use in Specific Populations (8.4)]

Children and Adolescents 6 through 16 Years of Age

The pharmacokinetics of PROTONIX Delayed-Release Tablets were evaluated in children ages 6 through 16 years with a clinical diagnosis of GERD. The PK parameters following a single oral dose of 20 mg or 40 mg of PROTONIX tablets in children ages 6 through 16 years were highly variable (%CV ranges 40 to 80%). The geometric mean AUC estimated from population PK analysis after a 40 mg PROTONIX tablet in pediatric patients was about 39% and 10% higher respectively in 6 to 11 and 12 to 16 year-old children, compared to that of adults (Table 7).

Table 7: PK Parameters in Children and Adolescents 6 through 16 years with GERD receiving 40 mg PROTONIX Tablets
 | 6–11 years (n=12) | 12–16 years (n=11)
Cmax (µg/mL) [Geometric mean values] | 1.8 | 1.8
tmax (h) [Median values] | 2.0 | 2.0
AUC (µg∙h/mL) | 6.9 | 5.5
CL/F (L/h) | 6.6 | 6.8

Male and Female Patients

There is a modest increase in pantoprazole AUC and Cmax in women compared to men. However, weight-normalized clearance values are similar in women and men.

In pediatric patients ages 1 through 16 years there were no clinically relevant effects of gender on clearance of pantoprazole, as shown by population pharmacokinetic analysis.

Patients with Renal Impairment

In patients with severe renal impairment, pharmacokinetic parameters for pantoprazole were similar to those of healthy subjects.

Patients with Hepatic Impairment

In patients with mild to severe hepatic impairment (Child-Pugh A to C cirrhosis), maximum pantoprazole concentrations increased only slightly (1.5-fold) relative to healthy subjects. Although serum half-life values increased to 7–9 hours and AUC values increased by 5- to 7-fold in hepatic-impaired patients, these increases were no greater than those observed in CYP2C19 poor metabolizers, where no dosage adjustment is warranted. These pharmacokinetic changes in hepatic-impaired patients result in minimal drug accumulation following once-daily, multiple-dose administration. Doses higher than 40 mg/day have not been studied in hepatically impaired patients.

Drug Interaction Studies

Effect of Other Drugs on Pantoprazole

Pantoprazole is metabolized mainly by CYP2C19 and to minor extents by CYPs 3A4, 2D6, and 2C9. In in vivo drug-drug interaction studies with CYP2C19 substrates (diazepam [also a CYP3A4 substrate] and phenytoin [also a CYP3A4 inducer] and clopidogrel), nifedipine, midazolam, and clarithromycin (CYP3A4 substrates), metoprolol (a CYP2D6 substrate), diclofenac, naproxen and piroxicam (CYP2C9 substrates), and theophylline (a CYP1A2 substrate) in healthy subjects, the pharmacokinetics of pantoprazole were not significantly altered.

Effect of Pantoprazole on Other Drugs

Clopidogrel

Clopidogrel is metabolized to its active metabolite in part by CYP2C19. In a crossover clinical study, 66 healthy subjects were administered clopidogrel (300 mg loading dose followed by 75 mg per day) alone and with pantoprazole (80 mg at the same time as clopidogrel) for 5 days. On Day 5, the mean AUC of the active metabolite of clopidogrel was reduced by approximately 14% (geometric mean ratio was 86%, with 90% CI of 79 to 93%) when pantoprazole was coadministered with clopidogrel as compared to clopidogrel administered alone. Pharmacodynamic parameters were also measured and demonstrated that the change in inhibition of platelet aggregation (induced by 5 µM ADP) was correlated with the change in the exposure to clopidogrel active metabolite. The clinical significance of this finding is not clear.

Mycophenolate Mofetil (MMF)

Administration of pantoprazole 40 mg twice daily for 4 days and a single 1000 mg dose of MMF approximately one hour after the last dose of pantoprazole to 12 healthy subjects in a cross-over study resulted in a 57% reduction in the Cmax and 27% reduction in the AUC of MPA. Transplant patients receiving approximately 2000 mg per day of MMF (n=12) were compared to transplant patients receiving approximately the same dose of MMF and pantoprazole 40 mg per day (n=21). There was a 78% reduction in the Cmax and a 45% reduction in the AUC of MPA in patients receiving both pantoprazole and MMF [see Drug Interactions (7)].

Other Drugs

In vivo studies also suggest that pantoprazole does not significantly affect the kinetics of the following drugs (cisapride, theophylline, diazepam [and its active metabolite, desmethyldiazepam], phenytoin, metoprolol, nifedipine, carbamazepine, midazolam, clarithromycin, diclofenac, naproxen, piroxicam, and oral contraceptives [levonorgestrel/ethinyl estradiol]). In other in vivo studies, digoxin, ethanol, glyburide, antipyrine, caffeine, metronidazole, and amoxicillin had no clinically relevant interactions with pantoprazole.

Although no significant drug-drug interactions have been observed in clinical studies, the potential for significant drug-drug interactions with more than once-daily dosing with high doses of pantoprazole has not been studied in poor metabolizers or individuals who are hepatically impaired.

Antacids

There was also no interaction with concomitantly administered antacids.

12.5 Pharmacogenomics

CYP2C19 displays a known genetic polymorphism due to its deficiency in some subpopulations (e.g., approximately 3% of Caucasians and African-Americans and 17% to 23% of Asians are poor metabolizers). Although these subpopulations of pantoprazole poor metabolizers have elimination half-life values of 3.5 to 10 hours in adults, they still have minimal accumulation (23% or less) with once-daily dosing. For adult patients who are CYP2C19 poor metabolizers, no dosage adjustment is needed.

Similar to adults, pediatric patients who have the poor metabolizer genotype of CYP2C19 (CYP2C19 *2/*2) exhibited greater than a 6-fold increase in AUC compared to pediatric extensive (CYP2C19 *1/*1) and intermediate (CYP2C19 *1/*x) metabolizers. Poor metabolizers exhibited approximately 10-fold lower apparent oral clearance compared to extensive metabolizers.

For known pediatric poor metabolizers, a dose reduction should be considered.

13 NONCLINICAL TOXICOLOGY

13.1 Carcinogenesis, Mutagenesis, Impairment of Fertility

In a 24-month carcinogenicity study, Sprague-Dawley rats were treated orally with pantoprazole doses of 0.5 to 200 mg/kg/day, about 0.1 to 40 times the exposure on a body surface area basis of a 50 kg person dosed with 40 mg/day. In the gastric fundus, treatment with 0.5 to 200 mg/kg/day produced enterochromaffin-like (ECL) cell hyperplasia and benign and malignant neuroendocrine cell tumors in a dose-related manner. In the forestomach, treatment with 50 and 200 mg/kg/day (about 10 and 40 times the recommended human dose on a body surface area basis) produced benign squamous cell papillomas and malignant squamous cell carcinomas. Rare gastrointestinal tumors associated with pantoprazole treatment included an adenocarcinoma of the duodenum with 50 mg/kg/day and benign polyps and adenocarcinomas of the gastric fundus with 200 mg/kg/day. In the liver, treatment with 0.5 to 200 mg/kg/day produced dose-related increases in the incidences of hepatocellular adenomas and carcinomas. In the thyroid gland, treatment with 200 mg/kg/day produced increased incidences of follicular cell adenomas and carcinomas for both male and female rats.

In a 24-month carcinogenicity study, Fischer 344 rats were treated orally with doses of 5 to 50 mg/kg/day of pantoprazole, approximately 1 to 10 times the recommended human dose based on body surface area. In the gastric fundus, treatment with 5 to 50 mg/kg/day produced enterochromaffin-like (ECL) cell hyperplasia and benign and malignant neuroendocrine cell tumors. Dose selection for this study may not have been adequate to comprehensively evaluate the carcinogenic potential of pantoprazole.

In a 24-month carcinogenicity study, B6C3F1 mice were treated orally with doses of 5 to 150 mg/kg/day of pantoprazole, 0.5 to 15 times the recommended human dose based on body surface area. In the liver, treatment with 150 mg/kg/day produced increased incidences of hepatocellular adenomas and carcinomas in female mice. Treatment with 5 to 150 mg/kg/day also produced gastric-fundic ECL cell hyperplasia.

A 26-week p53 +/- transgenic mouse carcinogenicity study was not positive.

Pantoprazole was positive in the in vitro human lymphocyte chromosomal aberration assays, in one of two mouse micronucleus tests for clastogenic effects, and in the in vitro Chinese hamster ovarian cell/HGPRT forward mutation assay for mutagenic effects. Equivocal results were observed in the in vivo rat liver DNA covalent binding assay. Pantoprazole was negative in the in vitro Ames mutation assay, the in vitro unscheduled DNA synthesis (UDS) assay with rat hepatocytes, the in vitro AS52/GPT mammalian cell-forward gene mutation assay, the in vitro thymidine kinase mutation test with mouse lymphoma L5178Y cells, and the in vivo rat bone marrow cell chromosomal aberration assay.

There were no effects on fertility or reproductive performance when pantoprazole was given at oral doses up to 500 mg/kg/day in male rats (98 times the recommended human dose based on body surface area) and 450 mg/kg/day in female rats (88 times the recommended human dose based on body surface area).

14 CLINICAL STUDIES

PROTONIX Delayed-Release Tablets were used in the following clinical trials.

14.1 Erosive Esophagitis (EE) Associated with Gastroesophageal Reflux Disease (GERD)

Adult Patients

A US multicenter, double-blind, placebo-controlled study of PROTONIX 10 mg, 20 mg, or 40 mg once daily was conducted in 603 patients with reflux symptoms and endoscopically diagnosed EE of grade 2 or above (Hetzel-Dent scale). In this study, approximately 25% of enrolled patients had severe EE of grade 3, and 10% had grade 4. The percentages of patients healed (per protocol, n = 541) in this study are shown in Table 8.

Table 8: Erosive Esophagitis Healing Rates (Per Protocol)
 |  | PROTONIX |  | Placebo
Week | 10 mg daily (n = 153) | 20 mg daily (n = 158) | 40 mg daily (n = 162) | (n = 68)
4 | 45.6% [(p < 0.001) PROTONIX versus placebo] | 58.4% [(p < 0.05) versus 10 mg PROTONIX] | 75.0% [(p < 0.05) versus 10 mg or 20 mg PROTONIX] | 14.3%
8 | 66.0% | 83.5% | 92.6% | 39.7%

In this study, all PROTONIX treatment groups had significantly greater healing rates than the placebo group. This was true regardless of H. pylori status for the 40 mg and 20 mg PROTONIX treatment groups. The 40 mg dose of PROTONIX resulted in healing rates significantly greater than those found with either the 20 mg or 10 mg dose.

A significantly greater proportion of patients taking PROTONIX 40 mg experienced complete relief of daytime and nighttime heartburn and the absence of regurgitation, starting from the first day of treatment, compared with placebo. Patients taking PROTONIX consumed significantly fewer antacid tablets per day than those taking placebo.

PROTONIX 40 mg and 20 mg once daily were also compared with nizatidine 150 mg twice daily in a US multicenter, double-blind study of 243 patients with reflux symptoms and endoscopically diagnosed EE of grade 2 or above. The percentages of patients healed (per protocol, n = 212) are shown in Table 9.

Table 9: Erosive Esophagitis Healing Rates (Per Protocol)
 | PROTONIX |  | Nizatidine
Week | 20 mg daily (n = 72) | 40 mg daily (n = 70) | 150 mg twice daily (n = 70)
4 | 61.4% [(p < 0.001) PROTONIX versus nizatidine] | 64.0% | 22.2%
8 | 79.2% | 82.9% | 41.4%

Once-daily treatment with PROTONIX 40 mg or 20 mg resulted in significantly superior rates of healing at both 4 and 8 weeks compared with twice-daily treatment with 150 mg of nizatidine. For the 40 mg treatment group, significantly greater healing rates compared to nizatidine were achieved regardless of the H. pylori status.

A significantly greater proportion of the patients in the PROTONIX treatment groups experienced complete relief of nighttime heartburn and regurgitation, starting on the first day and of daytime heartburn on the second day, compared with those taking nizatidine 150 mg twice daily. Patients taking PROTONIX consumed significantly fewer antacid tablets per day than those taking nizatidine.

Pediatric Patients Ages 5 Years through 16 Years

The efficacy of PROTONIX in the treatment of EE associated with GERD in pediatric patients ages 5 years through 16 years is extrapolated from adequate and well-conducted trials in adults, as the pathophysiology is thought to be the same. Four pediatric patients with endoscopically diagnosed EE were studied in multicenter, randomized, double-blind, parallel-treatment trials. Children with endoscopically diagnosed EE (defined as an endoscopic Hetzel-Dent score ≥2) were treated once daily for 8 weeks with one of two dose levels of PROTONIX (20 mg or 40 mg). All 4 patients with EE were healed (Hetzel-Dent score of 0 or 1) at 8 weeks.

14.2 Long-Term Maintenance of Healing of Erosive Esophagitis

Two independent, multicenter, randomized, double-blind, comparator-controlled trials of identical design were conducted in adult GERD patients with endoscopically confirmed healed EE to demonstrate efficacy of PROTONIX in long-term maintenance of healing. The two US studies enrolled 386 and 404 patients, respectively, to receive either 10 mg, 20 mg, or 40 mg of PROTONIX Delayed-Release Tablets once daily or 150 mg of ranitidine twice daily. As demonstrated in Table 10, PROTONIX 40 mg and 20 mg were significantly superior to ranitidine at every timepoint with respect to the maintenance of healing. In addition, PROTONIX 40 mg was superior to all other treatments studied.

Table 10: Long-Term Maintenance of Healing of Erosive Gastroesophageal Reflux Disease (GERD Maintenance): Percentage of Patients Who Remained Healed
 | PROTONIX 20 mg daily | PROTONIX 40 mg daily | Ranitidine 150 mg twice daily
Study 1 | n = 75 | n = 74 | n = 75
Month 1 | 91 [(p <0.05 vs. ranitidine)] | 99 | 68
Month 3 | 82 | 93 [(p <0.05 vs. PROTONIX 20 mg)] | 54
Month 6 | 76 | 90 | 44
Month 12 | 70 | 86 | 35
Study 2 | n = 74 | n = 88 | n = 84
Month 1 | 89 | 92 | 62
Month 3 | 78 | 91 | 47
Month 6 | 72 | 88 | 39
Month 12 | 72 | 83 | 37
Note: PROTONIX 10 mg was superior (p <0.05) to ranitidine in Study 2, but not Study 1.

PROTONIX 40 mg was superior to ranitidine in reducing the number of daytime and nighttime heartburn episodes from the first through the twelfth month of treatment. PROTONIX 20 mg, administered once daily, was also effective in reducing episodes of daytime and nighttime heartburn in one trial, as presented in Table 11.

Table 11: Number of Episodes of Heartburn (mean ± SD)
 |  | PROTONIX 40 mg daily | Ranitidine 150 mg twice daily
Month 1 | Daytime | 5.1 ± 1.6 [(p <0.001 vs. ranitidine, combined data from the two US studies)] | 18.3 ± 1.6
 | Nighttime | 3.9 ± 1.1 | 11.9 ± 1.1
Month 12 | Daytime | 2.9 ± 1.5 | 17.5 ± 1.5
 | Nighttime | 2.5 ± 1.2 | 13.8 ± 1.3

14.3 Pathological Hypersecretory Conditions Including Zollinger-Ellison Syndrome

In a multicenter, open-label trial of 35 patients with pathological hypersecretory conditions, such as Zollinger-Ellison Syndrome, with or without multiple endocrine neoplasia-type I, PROTONIX successfully controlled gastric acid secretion. Doses ranging from 80 mg daily to 240 mg daily maintained gastric acid output below 10 mEq/h in patients without prior acid-reducing surgery and below 5 mEq/h in patients with prior acid-reducing surgery.

Doses were initially titrated to the individual patient needs, and adjusted in some patients based on the clinical response with time [see Dosage and Administration (2)]. PROTONIX was well tolerated at these dose levels for prolonged periods (greater than 2 years in some patients).

16 HOW SUPPLIED/STORAGE AND HANDLING

How Supplied

PROTONIX (pantoprazole sodium) For Delayed-Release Oral Suspension is supplied as pale yellowish to dark brownish, enteric-coated granules containing 40 mg pantoprazole in a unit-dose packet and are available as follows:

Overbagged with 10 packets per bag, NDC 55154-4232-0

Storage

Store PROTONIX For Delayed-Release Oral Suspension and PROTONIX Delayed-Release Tablets at 20° to 25°C (68° to 77°F); excursions permitted to 15° to 30°C (59° to 86°F) [see USP Controlled Room Temperature].

17 PATIENT COUNSELING INFORMATION

Advise the patient to read the FDA-approved patient labeling (Medication Guide and Instructions for Use).

Gastric Malignancy

Advise patients to return to their healthcare provider if they have a suboptimal response or an early symptomatic relapse [see Warnings and Precautions (5.1)].

Acute Tubulointerstitial Nephritis

Advise patients to call their healthcare provider immediately if they experience signs and/or symptoms associated with acute tubulointerstitial nephritis [see Contraindications (4), Warnings and Precautions (5.2)].

Clostridium difficile-Associated Diarrhea

Advise patients to immediately call their healthcare provider if they experience diarrhea that does not improve [see Warnings and Precautions (5.3)].

Bone Fracture

Advise patients to report any fractures, especially of the hip, wrist or spine, to their healthcare provider [see Warnings and Precautions (5.4)].

Severe Cutaneous Adverse Reactions

Advise patients to discontinue PROTONIX and immediately call their healthcare provider for further evaluation [see Warnings and Precautions (5.5)].

Cutaneous and Systemic Lupus Erythematosus

Advise patients to immediately call their healthcare provider for any new or worsening of symptoms associated with cutaneous or systemic lupus erythematosus [see Warnings and Precautions (5.6)].

Cyanocobalamin (Vitamin B-12) Deficiency

Advise patients to report any clinical symptoms that may be associated with cyancobalamin deficiency to their healthcare provider if they have been receiving PROTONIX for longer than 3 years [see Warnings and Precautions (5.7)].

Hypomagnesemia and Mineral Metabolism

Advise patients to report any clinical symptoms that may be associated with hypomagnesemia, hypocalcemia, and/or hypokalemia, to their healthcare provider, if they have been receiving PROTONIX for at least 3 months [see Warnings and Precautions (5.8)].

Drug Interactions

Instruct patients to inform their healthcare provider of any other medications they are currently taking, including rilpivirine-containing products [see Contraindications (4)], digoxin [see Warnings and Precautions (5.8)] and high dose methotrexate [see Warnings and Precautions (5.13)].

Pregnancy

Advise a pregnant woman of the potential risk to a fetus. Advise females of reproductive potential to inform their healthcare provider of a known or suspected pregnancy [see Use in Specific Populations (8.1)].

Administration

- Do not split, crush, or chew PROTONIX For Delayed-Release Oral Suspension and PROTONIX Delayed-Release Tablets.
- PROTONIX oral suspension packet is a fixed dose and cannot be divided to make a smaller dose.
- Swallow PROTONIX Delayed-Release Tablets whole, with or without food in the stomach.
- Concomitant administration of antacids does not affect the absorption of PROTONIX Delayed-Release Tablets.
- Take PROTONIX For Delayed-Release Oral Suspension approximately 30 minutes before a meal.
- Administer PROTONIX For Delayed-Release Oral Suspension in apple juice or applesauce, as described in the Instructions for Use. Do not administer in water, other liquids, or foods.
- For patients with a nasogastric (NG) or gastrostomy tube, PROTONIX For Delayed-Release Oral Suspension can be administered with apple juice, as described in the Instructions for Use.
- Take a missed dose as soon as possible. If it is almost time for the next dose, skip the missed dose and take the next dose at the regular scheduled time. Do not take 2 doses at the same time.

This product's label may have been updated. For the most recent prescribing information, please visit www.pfizer.com.

For Medical Information about PROTONIX, please visit www.pfizermedinfo.com or call 1-800-438-1985.

under license from
Takeda GmbH
D78467 Konstanz, Germany

Distributed By:

Cardinal Health

Dublin, OH 43017

L45542750324

LAB-0459-21.0

MEDICATION GUIDE
PROTONIX (pro-TAH-nix)
(pantoprazole sodium)
delayed-release tablets
and
PROTONIX (pro-TAH-nix)
(pantoprazole sodium)
for delayed-release oral suspension

What is the most important information I should know about PROTONIX?
You should take PROTONIX exactly as prescribed, at the lowest dose possible and for the shortest time needed.
PROTONIX may help your acid-related symptoms, but you could still have serious stomach problems. Talk with your doctor.
PROTONIX can cause serious side effects, including:

- A type of kidney problem (acute tubulointerstitial nephritis). Some people who take proton pump inhibitor (PPI) medicines, including PROTONIX, may develop a kidney problem called acute tubulointerstitial nephritis that can happen at any time during treatment with PROTONIX. Call your doctor right away if you have a decrease in the amount that you urinate or if you have blood in your urine.
- Diarrhea caused by an infection (Clostridium difficile) in your intestines. Call your doctor right away if you have watery stools or stomach pain that does not go away. You may or may not have a fever.
- Bone fractures (hip, wrist, or spine). Bone fractures in the hip, wrist, or spine may happen in people who take multiple daily doses of PPI medicines and for a long period of time (a year or longer). Tell your doctor if you have a bone fracture, especially in the hip, wrist, or spine.
- Certain types of lupus erythematosus. Lupus erythematosus is an autoimmune disorder (the body's immune cells attack other cells or organs in the body). Some people who take PPI medicines, including PROTONIX, may develop certain types of lupus erythematosus or have worsening of the lupus they already have. Call your doctor right away if you have new or worsening joint pain or a rash on your cheeks or arms that gets worse in the sun.
- Low magnesium and other mineral levels in your body can happen in people who have taken PROTONIX for at least 3 months. Tell your doctor if you have symptoms of low magnesium levels, including seizures, dizziness, irregular heartbeat, jitteriness, muscle aches or weakness, and spasms of hands, feet or voice.

Talk to your doctor about your risk of these serious side effects.
PROTONIX can have other serious side effects. See "What are the possible side effects of PROTONIX?"

What is PROTONIX?
A prescription medicine called a proton pump inhibitor (PPI) used to reduce the amount of acid in your stomach.
In adults, PROTONIX is used for:

- up to 8 weeks for the healing and symptom relief of acid-related damage to the lining of the esophagus (called erosive esophagitis or EE). Your doctor may prescribe another 8 weeks of PROTONIX in patients whose EE does not heal.
- maintaining healing of EE and to help prevent the return of heartburn symptoms caused by GERD. It is not known if PROTONIX is safe and effective when used for longer than 12 months for this purpose.
- the long-term treatment of conditions where your stomach makes too much acid. This includes a rare condition called Zollinger-Ellison Syndrome.

In children 5 years of age and older, PROTONIX is used for:

- up to 8 weeks for the healing and symptom relief of EE.
  It is not known if PROTONIX is safe if used longer than 8 weeks in children.

PROTONIX is not for use in children under 5 years of age.
It is not known if PROTONIX is safe and effective in children for treatment other than EE.

Do not take PROTONIX if you are:

- allergic to pantoprazole sodium, any other PPI medicine, or any of the ingredients in PROTONIX. See the end of this Medication Guide for a complete list of ingredients.
- taking a medicine that contains rilpivirine (EDURANT, COMPLERA, ODEFSEY, JULUCA) used to treat HIV-1 (Human Immunodeficiency Virus).

Before taking PROTONIX, tell your doctor about all of your medical conditions, including if you:

- have low magnesium levels, low calcium levels and low potassium levels in your blood.
- are pregnant or plan to become pregnant. PROTONIX may harm your unborn baby. Tell your doctor if you become pregnant or think you may be pregnant during treatment with PROTONIX.
- are breastfeeding or plan to breastfeed. PROTONIX can pass into your breast milk. Talk with your doctor about the best way to feed your baby if you take PROTONIX.

Tell your doctor about all the medicines you take, including prescription and over-the-counter medicines, vitamins and herbal supplements. Especially tell your doctor if you take methotrexate (Otrexup, Rasuvo, Trexall, XATMEP), digoxin (LANOXIN), or a water pill (diuretic).

How should I take PROTONIX?

- Take PROTONIX exactly as prescribed by your doctor.
  PROTONIX delayed-release tablets (PROTONIX tablets):
  - Do not split, chew, or crush PROTONIX tablets.
  - Swallow PROTONIX tablets whole, with or without food.
  - Tell your doctor if you are not able to swallow your PROTONIX tablet.
PROTONIX for delayed-release oral suspension (PROTONIX for oral suspension):
  1. You may use antacids while taking PROTONIX tablets.
  2. Do not split, chew, or crush PROTONIX for oral suspension.
  3. Take PROTONIX for oral suspension about 30 minutes before a meal.
  4. PROTONIX for oral suspension should only be given by mouth mixed in apple juice or applesauce or through a nasogastric (NG) tube or gastrostomy tube mixed in apple juice. Do not mix PROTONIX for oral suspension in liquids other than apple juice or foods other than applesauce.
  5. Do not divide a packet of PROTONIX for oral suspension to make a smaller dose.
  6. See the "Instructions for Use" at the end of this Medication Guide for instructions on how to mix and take PROTONIX for oral suspension by mouth in applesauce or apple juice or how to mix and give the suspension through an NG tube or gastrostomy tube mixed in apple juice.
- If you miss a dose of PROTONIX, take it as soon as possible. If it is almost time for your next dose, do not take the missed dose. Take the next dose at your regular time. Do not take 2 doses at the same time.
- If you take too much PROTONIX, call your doctor or your poison control center at 1-800-222-1222 right away or go to the nearest emergency room.

What are the possible side effects of PROTONIX?
PROTONIX can cause serious side effects, including:

- See "What is the most important information I should know about PROTONIX?"
- Low vitamin B-12 levels in your body can happen in people who have taken PROTONIX for a long time (more than 3 years). Tell your doctor if you have symptoms of low vitamin B-12 levels, including shortness of breath, lightheadedness, irregular heartbeat, muscle weakness, pale skin, feeling tired, mood changes, and tingling or numbness in the arms and legs.
- Stomach growths (fundic gland polyps). People who take PPI medicines for a long time have an increased risk of developing a certain type of stomach growths called fundic gland polyps, especially after taking PPI medicines for more than 1 year.
- Severe skin reactions. PROTONIX can cause rare but severe skin reactions that may affect any part of your body. These serious skin reactions may need to be treated in a hospital and may be life threatening:
  - Skin rash which may have blistering, peeling or bleeding on any part of your skin (including your lips, eyes, mouth, nose, genitals, hands or feet).
  - You may also have fever, chills, body aches, shortness of breath, or enlarged lymph nodes.

Stop taking PROTONIX and call your doctor right away. These symptoms may be the first sign of a severe skin reaction.
The most common side effects of PROTONIX in adults include: headache, diarrhea, nausea, stomach-area (abdominal) pain, vomiting, gas, dizziness, and joint pain.
The most common side effects of PROTONIX in children include: upper respiratory infection, headache, fever, diarrhea, vomiting, rash, and stomach-area (abdominal) pain.
These are not all the possible side effects of PROTONIX. Call your doctor for medical advice about side effects. You may report side effects to FDA at 1-800-FDA-1088.

How should I store PROTONIX?
Store PROTONIX at room temperature between 68°F to 77°F (20°C to 25°C).
Keep PROTONIX and all medicines out of the reach of children.

General information about the safe and effective use of PROTONIX.
Medicines are sometimes prescribed for purposes other than those listed in a Medication Guide. Do not use PROTONIX for a condition for which it was not prescribed. Do not give PROTONIX to other people, even if they have the same symptoms that you have. It may harm them. You can ask your doctor or pharmacist for information about PROTONIX that is written for health professionals.

What are the ingredients in PROTONIX?
Active ingredient: pantoprazole sodium sesquihydrate
Inactive ingredients in PROTONIX delayed-release tablets: calcium stearate, crospovidone, hypromellose, iron oxide, mannitol, methacrylic acid copolymer, polysorbate 80, povidone, propylene glycol, sodium carbonate, sodium lauryl sulfate, titanium dioxide, and triethyl citrate.
Inactive ingredients in PROTONIX for delayed-release oral suspension: crospovidone, hypromellose, methacrylic acid copolymer, microcrystalline cellulose, polysorbate 80, povidone, sodium carbonate, sodium lauryl sulfate, talc, titanium dioxide, triethyl citrate, and yellow ferric oxide.
For more information go to www.pfizer.com or call 1-800-438-1985.

This Medication Guide has been approved by the U.S. Food and Drug Administration.

This product's label may have been updated. For the most recent prescribing information, please go to www.pfizer.com.

under license from
Takeda GmbH
D78467 Konstanz, Germany

Distributed By:

Cardinal Health

Dublin, OH 43017

L45542750324

LAB-0574-16.0

Revised: March 2022

Instructions for Use PROTONIX (pro-TAH-nix) (pantoprazole sodium) for delayed-release oral suspension

PROTONIX for delayed-release oral suspension (PROTONIX for oral suspension):

Important information:

- Do not split, chew, or crush PROTONIX for oral suspension.
- Take PROTONIX for oral suspension about 30 minutes before a meal.
- PROTONIX for oral suspension:
  - should only be taken with applesauce or apple juice.
  - should not be mixed in water or other liquids, or other foods.
  - packet should not be divided to make a smaller dose.
- Taking PROTONIX for oral suspension with applesauce:
  - Open the packet of PROTONIX for oral suspension.
  - Sprinkle all of the granules in the packet on 1 teaspoon of applesauce.
  - Swallow the granules and applesauce within 10 minutes of putting the granules on the teaspoon of applesauce.
  - Take sips of water to make sure the granules are washed down into the stomach. Take more sips of water as needed.
- Taking PROTONIX for oral suspension with apple juice:
  - Open the packet of PROTONIX for oral suspension.
  - Empty all of the granules in the packet into a small cup that contains 1 teaspoon of apple juice.
  - Stir the granules-apple juice mixture for 5 seconds. The granules will not break up.
  - Swallow the mixture right away.
  - To make sure that the entire dose is taken, add more apple juice to the cup, stir and swallow the apple juice right away.
  - Repeat step 5 if there are granules left in the cup.
- Giving PROTONIX for oral suspension through a nasogastric (NG) tube or gastrostomy tube:
  - PROTONIX for oral suspension may be given through an NG tube or gastrostomy tube that is size 16 French or larger. Do not give PROTONIX for oral suspension through an NG tube or gastrostomy tube smaller than size 16 French.
  - Mix PROTONIX for oral suspension only in apple juice when giving through an NG tube or gastrostomy tube.
    - Remove the plunger from a 60 mL (2 ounce) catheter-tip syringe. Throw away the plunger.
    - Connect the tip of the catheter-tip syringe to the NG tube or gastrostomy tube.
    - Hold the syringe attached to the NG tube or gastrostomy tube as high as possible while giving PROTONIX for oral suspension to prevent the tubing from bending.
    - Open the packet of PROTONIX for oral suspension.
    - Empty all the granules in the packet into the catheter-tip syringe.
    - Add 10 mL (2 teaspoons) of apple juice into the catheter-tip syringe and gently tap or shake the syringe to help empty the syringe.
    - Repeat step 6 at least 2 more times until there are no granules left in the catheter-tip syringe.

How should I store PROTONIX?

Store PROTONIX at room temperature between 68°F to 77°F (20°C to 25°C).

Keep PROTONIX and all medicines out of the reach of children.

This Instructions for Use has been approved by the U.S. Food and Drug Administration.

This product's label may have been updated. For the most recent prescribing information, please go to www.pfizer.com.

under license from
Takeda GmbH
D78467 Konstanz, Germany

Distributed By:

Cardinal Health

Dublin, OH 43017

L45542750324

LAB-1511-1.0

Revised: March 2022

Package/Label Display Panel

PROTONIX® 40 mg

Pantoprazole Sodium

For Delayed-Release Oral Suspension*

10 PACKETS